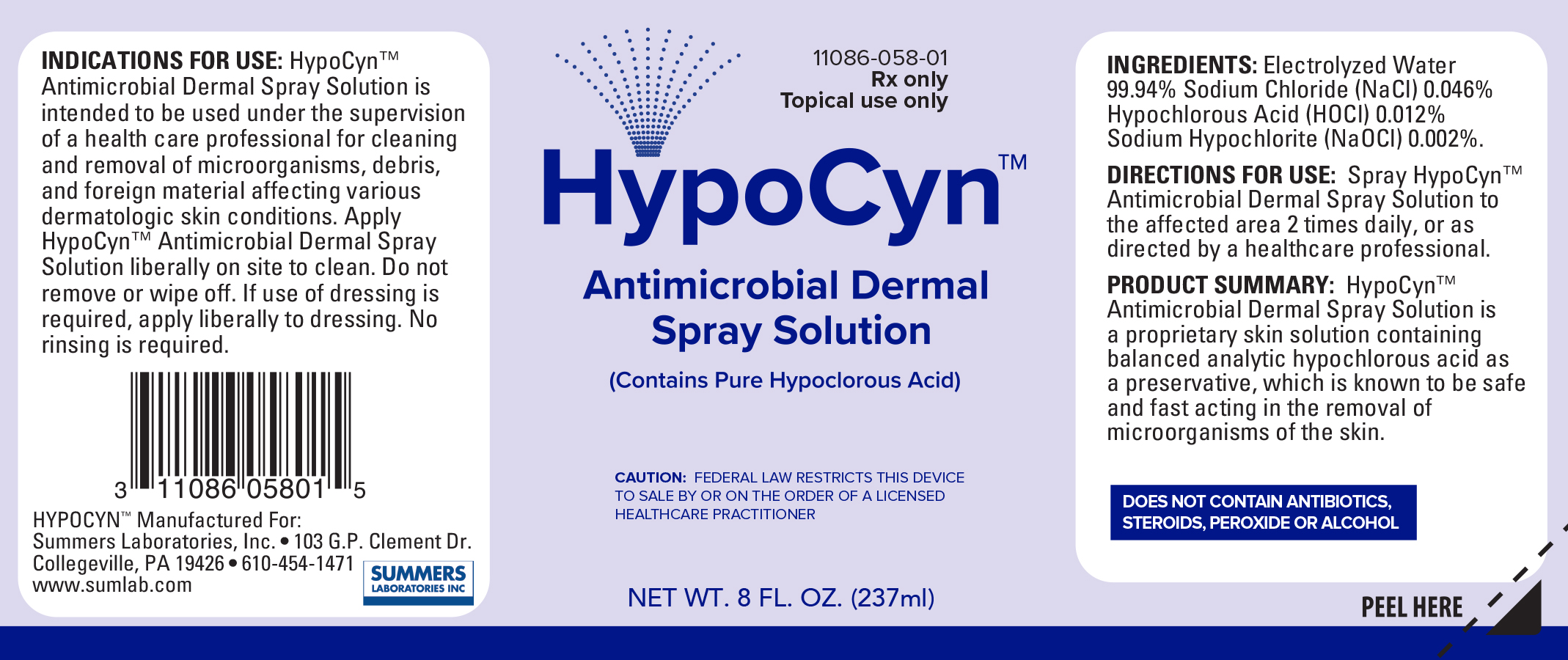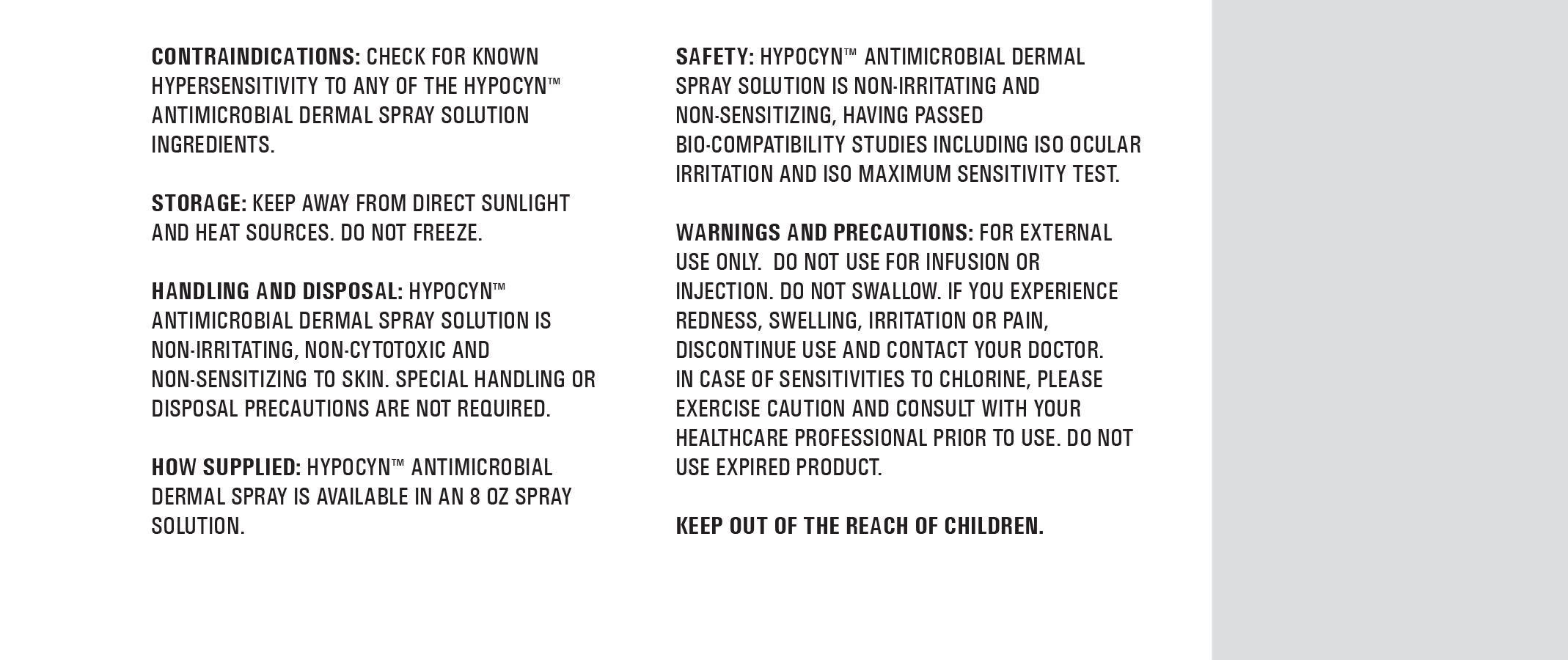 DRUG LABEL: HypoCyn
NDC: 11086-058
Manufacturer: Summers Laboratories, Inc.
Category: other | Type: PRESCRIPTION MEDICAL DEVICE LABEL
Date: 20220314

HypoCyn™
Antimicrobial Dermal Spray Solution

INDICATIONS FOR USE:

HypoCyn™ Antimicrobial Dermal Spray Solution is intended to be used under the supervison of a health care professional for cleaning and removal of microorganisms, debris, and foreign material affecting various dermatologic skin conditions. Apply HypoCynTM Antimicrobial Dermal Spray Solution liberally on site to clean. Do not remove or wipe off. If use of dressing is required, apply liberally to dressing. No rinsing is required.

DIRECTIONS FOR USE:

Spray HypoCyn™ Antimicrobial Dermal Spray Solution to the affected area 2 times daily, or as directed by a healthcare professional.

DESCRIPTION:

HypoCyn™ Antimicrobial Dermal Spray Solution is a proprietary skin solution containing balanced analytic hypochlorous acid as a preservitive, which is know to be safe and fast acting in the removal of microorganisms of the skin.

CONTRAINDICATIONS:

Check for known hypersensitivity to any of the HypoCyn™ Antimicrobial Dermal Spray Solution ingredients.

STORAGE:

Keep away from direct sunlight and heat sources. Do Not Freeze.

HANDLING AND DISPOSAL:

HypoCyn™ Antimicrobial Dermal Spray Solution is non-irritating, non-cytotoxic and non-sensitizing to skin. Special handling or disposal precautions are not required.

SAFETY:

HypoCyn™ Antimicrobial Dermal Spray Solution is non-irritating and non-sensitizing, having passed bio-compatibility studies including ISO ocular irritation and ISO Maximum Sensitivity test.

WARNINGS AND PRECAUTIONS:

For external use only. Do not use for infusion or injection. Do not swallow. If you experience redness, swelling, irritation or pain, discontinue use and contact your doctor. In case of sensitivities to chlorine, please exercise caution and consult with your doctor prior to use. Do not use expired product.

HOW SUPPLIED:

HypoCyn™ Antimicrobial Dermal Spray Solution is supplied in an 8 fl. oz. (237ml) bottle.

KEEP OUT OF THE REACH OF CHILDREN.

DOES NOT CONTAIN ANTIBIOTICS, STEROIDS, PEROXIDE OR ALCOHOL